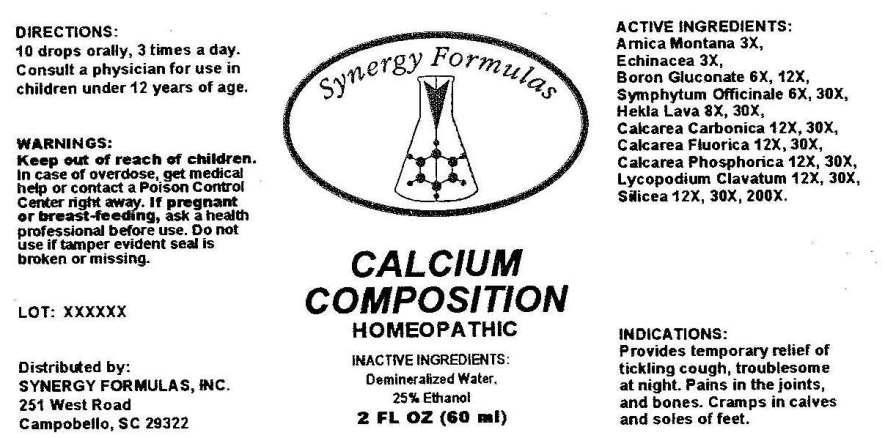 DRUG LABEL: Calcium Composition
NDC: 43772-0037 | Form: LIQUID
Manufacturer: Synergy Formulas, Inc
Category: homeopathic | Type: HUMAN OTC DRUG LABEL
Date: 20140716

ACTIVE INGREDIENTS: ARNICA MONTANA 3 [hp_X]/1 mL; ECHINACEA ANGUSTIFOLIA 3 [hp_X]/1 mL; BORON GLUCONATE 6 [hp_X]/1 mL; COMFREY ROOT 6 [hp_X]/1 mL; HEKLA LAVA 8 [hp_X]/1 mL; OYSTER SHELL CALCIUM CARBONATE, CRUDE 12 [hp_X]/1 mL; CALCIUM FLUORIDE 12 [hp_X]/1 mL; TRIBASIC CALCIUM PHOSPHATE 12 [hp_X]/1 mL; LYCOPODIUM CLAVATUM SPORE 12 [hp_X]/1 mL; SILICON DIOXIDE 12 [hp_X]/1 mL
INACTIVE INGREDIENTS: WATER; ALCOHOL

DRUG FACTS

ACTIVE INGREDIENTS:

Arnica Montana 3X, Echinacea (Angustifolia) 3X, Boron Gluconate 6X, 12X, Symphytum Officinale 6X, 30X, Hekla Lava 8X, 30X, Calcarea Carbonica 12X, 30X, Calcarea Fluorica 12X, 30X, Calcarea Phosphorica 12X, 30X, Lycopodium Clavatum 12X, 30X, Silicea 12X, 30X, 200X

INDICATIONS:

Provides temporary relief of tickling cough, troublesome at night. Pains in the joints, and bones. Cramps in calves and soles of feet.

WARNINGS:

Keep out of reach of children. In case of overdose, get medical help or contact a Poison Control Center right away.

If pregnant or breast-feeding, ask a health professional before use.

Do not use if tamper evident seal is broken or missing.

KEEP OUT OF REACH OF CHILDREN. In case of overdose, get medical help or contact a Poison Control Center right away.

DIRECTIONS:

10 drops orally, 3 times a day. Consult a physician for use in children under 12 years of age.

INDICATIONS:

Provides temporary relief of tickling cough, troublesome at night. Pains in the joints, and bones. Cramps in calves and soles of feet.

INACTIVE INGREDIENTS:

Demineralized Water, 25% Ethanol

QUESTIONS:

Distributed by:

SYNERGY FORMULAS, INC

251 West Road

Campobello, SC 29322

PACKAGE LABEL DISPLAY:

Synergy Formulas

CALCIUM COMPOSITION

HOMEOPATHIC

2 FL OZ (60 ml)